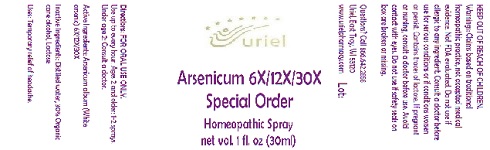 DRUG LABEL: Arsenicum 6/12/30 Special Order
NDC: 48951-1291 | Form: SPRAY
Manufacturer: Uriel Pharmacy Inc.
Category: homeopathic | Type: HUMAN OTC DRUG LABEL
Date: 20180503

ACTIVE INGREDIENTS: ARSENIC TRIOXIDE 6 [hp_X]/1 mL
INACTIVE INGREDIENTS: WATER; ALCOHOL; LACTOSE, UNSPECIFIED FORM

Arsenicum 6/12/30 Special Order

INDICATIONS AND USAGE

Directions: FOR ORAL USE ONLY.

DOSAGE AND ADMINISTRATION

Use up to every hour. Ages 2 and older: 1-2 sprays. Under age 2: Consult a doctor.

ACTIVE INGREDIENT

Active Ingredients: Arsenicum album (White arsenic) 6X/12X/30X

INACTIVE INGREDIENT

Inactive Ingredients: Distilled water, 30% Organic cane alcohol, Lactose

PURPOSE

Uses: Temporary relief of headache.

KEEP OUT OF REACH OF CHILDREN.

WARNINGS

Warnings: Claims based on traditional homeopathic practice, not accepted medical evidence. Not FDA evaluated. Do not use if allergic to any ingredient. Consult a doctor before use for serious conditions or if conditions worsen or persist. Contains traces of lactose. If pregnant or nursing, consult a doctor before use. Avoid contact with eyes. Do not use if safety seals on box are broken or missing.

Questions? Call 866.642.2858
Uriel, East Troy, WI 53120
www.urielpharmacy.com